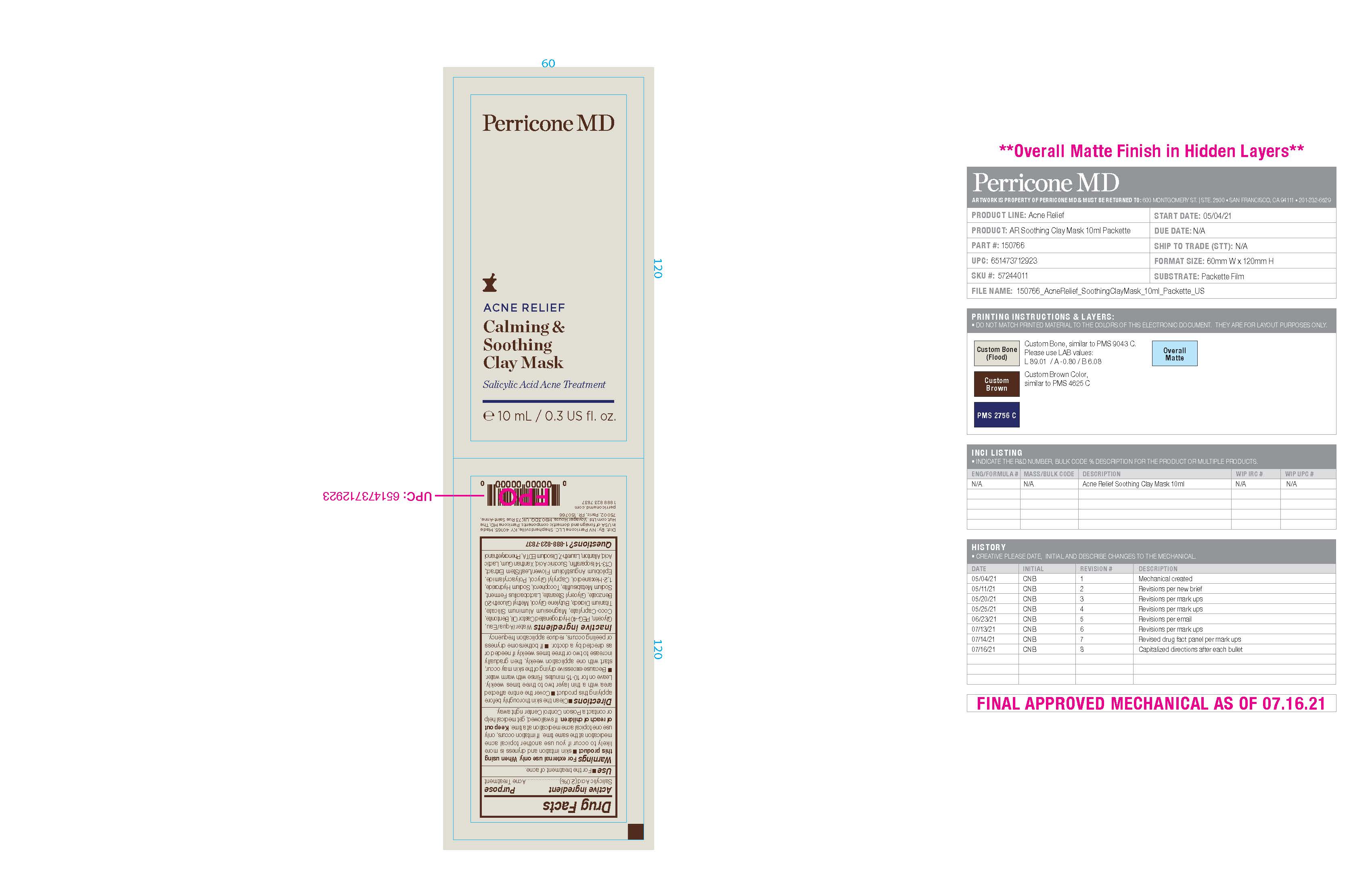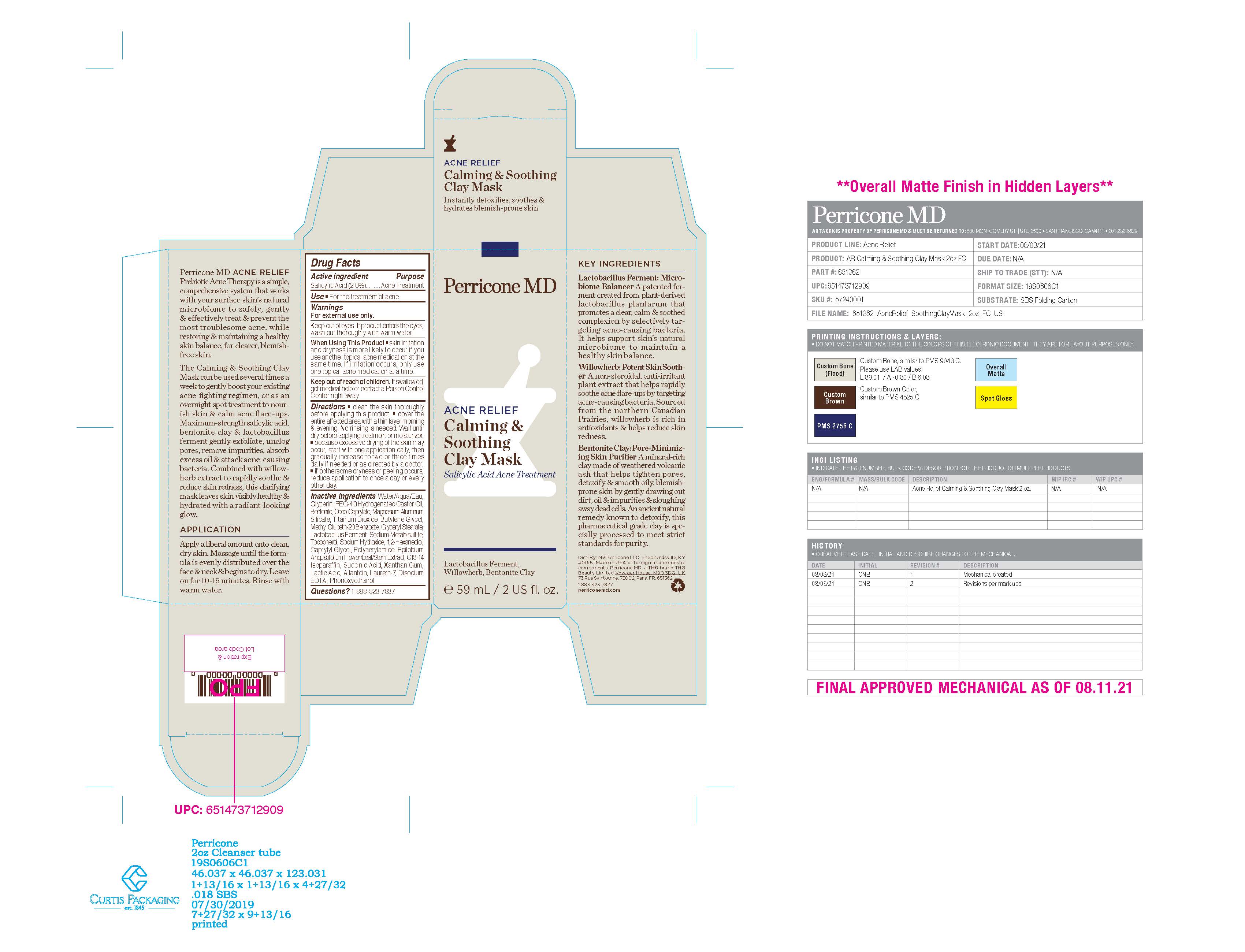 DRUG LABEL: Perricone MD Acne Relief Calming and Soothing Clay Mask
NDC: 84448-955 | Form: CREAM
Manufacturer: THG Beauty USA LLC
Category: otc | Type: HUMAN OTC DRUG LABEL
Date: 20251114

ACTIVE INGREDIENTS: SALICYLIC ACID 2 g/100 mL
INACTIVE INGREDIENTS: SODIUM HYDROXIDE; XANTHAN GUM; WATER; GLYCERIN; GLYCERYL MONOSTEARATE; METHYL GLUCETH-20; POLYACRYLAMIDE (CROSSLINKED; 2 MOLE PERCENT BISACRYLAMIDE); LAURETH-7; TITANIUM DIOXIDE; C13-14 ISOPARAFFIN; EPILOBIUM ANGUSTIFOLIUM WHOLE; EDETATE DISODIUM; LIMOSILACTOBACILLUS FERMENTUM; 1,2-HEXANEDIOL; ALLANTOIN; BENTONITE; SODIUM METABISULFITE; SUCCINIC ACID; PHENOXYETHANOL; MAGNESIUM ALUMINUM SILICATE; CAPRYLYL GLYCOL; COCO-CAPRYLATE; LACTIC ACID; TOCOPHEROL; POLYOXYL 40 HYDROGENATED CASTOR OIL; BUTYLENE GLYCOL

ACTIVE INGREDIENT

Salicylic Acid

PURPOSE

Acne Treatment

INDICATIONS AND USAGE

For the treatment of acne

WARNINGS

For external use only.

When using this product

- Skin irritation and dryness is more likely to occur if you use another topical acne medication at the same time. If irritation occurs, only use one topical acne medication at a time.

Keep out of reach of children. If swallowed, get medical help or contact a Poison Control Centre right away

DOSAGE AND ADMINISTRATION

■ Clean the skin thoroughly before applying this product.

■ Cover the entire affected area with a thin layer two to three times weekly. Leave on for 10-15 minutes. Rinse with warm water.

■ Because excessive drying of the skin may occur, start with one application weekly, then gradually increase to two or three times weekly if needed or as directed by a doctor.

■ If bothersome dryness or peeling occurs, reduce application frequency.

INACTIVE INGREDIENT

Water/Aqua/Eau, Glycerin, PEG-40 Hydrogenated Castor Oil, Bentonite, Coco-Caprylate, Magnesium Aluminum Silicate, Titanium Dioxide, Butylene Glycol, Methyl Gluceth-20 Benzoate, Glyceryl Stearate, Lactobacillus Ferment, Sodium Metabisulfite, Tocopherol, Sodium Hydroxide, 1,2-Hexanediol, Caprylyl Glycol, Polyacrylamide, Epilobium Angustifolium Flower/Leaf/Stem Extract, C13-14
Isoparaffin, Succinic Acid, Xanthan Gum, Lactic Acid, Allantoin, Laureth-7, Disodium EDTA, Phenoxyethanol

QUESTIONS

1-888-823-7837